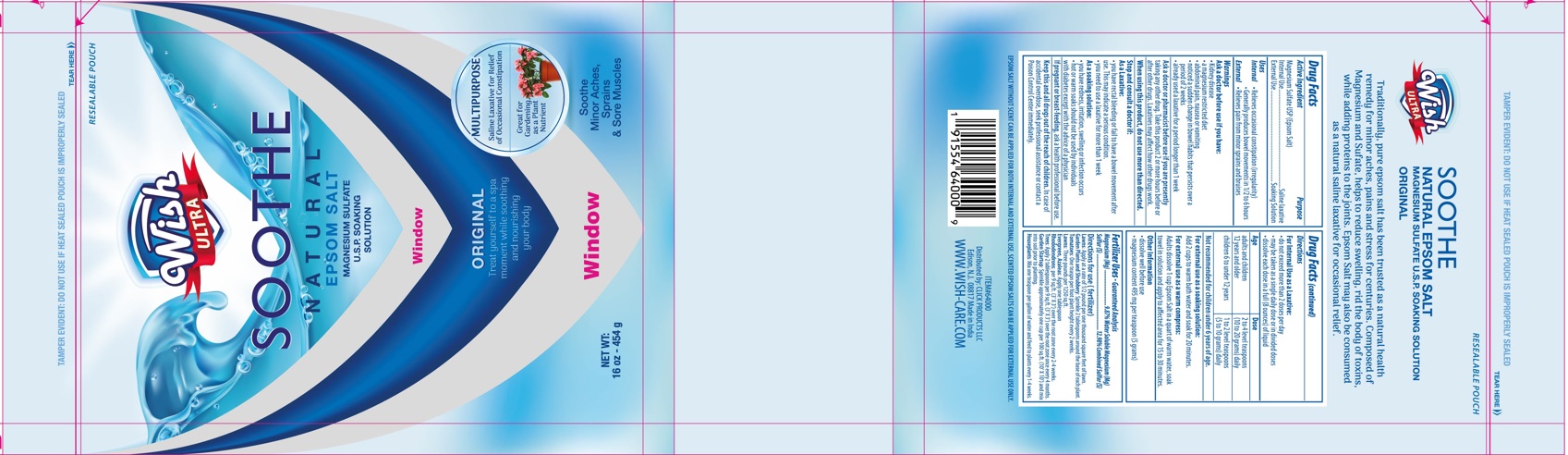 DRUG LABEL: Wish Ultra Natural Epsom Salt
NDC: 71611-025 | Form: GRANULE, FOR SOLUTION
Manufacturer: CLICK PRODUCTS LLC
Category: otc | Type: HUMAN OTC DRUG LABEL
Date: 20211011

ACTIVE INGREDIENTS: MAGNESIUM SULFATE, UNSPECIFIED 1 g/1 g
INACTIVE INGREDIENTS: WATER

Wish Ultra Soothe Natural Epsom Salt

Active Ingredient

Magnesium Sulfate USP (Epsom Salt)

Purpose

Internal Use.......... Saline Laxative

External Use..........Soaking Solution

INDICATIONS AND USAGE

Uses (Internal)

- Relieves occasional constipation (irregularity)
- Generally produces bowel movements in 1/2 to 6 hours

Uses (External)

- Relieves pain from major sprains and bruises

Warnings - Ask a doctor before use if you have:

- Kidney disease
- a magnesium restricted diet
- abdominal pain, nausea or vomiting
- noticed a sudden change in bowel habbits that persists over a period of 2 weeks
- already used a laxative for a period longer than 1 week

Ask a doctor or pharmacist before use if you are presently taking any other drug. Take this product 2 or more hours before or after other drugs. Laxatives may affect how other drugs work.

Stop and consult a doctor if:

As Laxative:

- you have rectal bleeding or fail to have a bowel movement after use. This may indicate a serious condition
- you need to use a laxative for more than 1 week

As soaking solution:

- you have redness, irritation, swelling or infection occurs
- hot or warm soaks should not be used by individuals with diabeties except with the advice of a physician

PREGNANCY OR BREAST FEEDING

If pregnant or breast-feeding, ask a health profesional before use.

KEEP OUT OF REACH OF CHILDREN

Keep this and all drugs out of the reach of children. In the case of an accidental overdose, seek professional assistance or contact Poison Control Center immedietly.

EPSOM SALT WITHOUT SCENT CAN BE APPLIED FOR BOTH INTERNAL AND EXTERNAL USE,
SCENTED EPSOM SALTS CAN BE APPLIED FOR EXTERNAL USE ONLY

INDICATIONS AND USAGE

Directions for Internal Use as a Laxative

- do not exceed more than 2 doses per day
- may be taken as a single daily dose or in divided doses
- dissolve each dose in a full (8 ounces) of liquid

Age | Dose
adults and children 12 years and older | 2 to 4 level teaspoons (10 to 20 grams) daily
children 6 to under 12 years | 1 to 2 level teaspoons (5 to 10 grams) daily

Not recomended for children under 6 years of age

DOSAGE AND ADMINISTRATION

SORE FEET RELIEF: Add one cup of HealthSmartTM Epsom Salt to one gallon of warm water and soak at least 5 minutes at a time.

BATH SOAK: Add two cups of HealthSmartTM Epsom salt under warm running bath water to release its gentle aroma. HealthSmartTM Epsom Salt helps relieve tension and provides a soothing, relaxing experience. Soak for at least 20 minutes.

First Aid Compress: Dissolve 2 cups of HealthSmartTM Epsom Salt into two cups of hot water to make a compress, apply as a wet dressing with a towel to:soothe bruises & sprains, take the sting out of insect bites, draw out splinters, alleviate pain from sports and overexertion.

Keep out of reach of children Where promt relief is not obtained or where there is evidence of infection, discontinue use and consult a physician. Hot or warm soaks should not be used by individuals with diabetes except on advice of a physician. Avoid contact with eyes.

EPSOM SALT WITHOUT SCENT CAN BE APPLIED FOR BOTH INTERNAL AND EXTERNAL USE, SCENTED EPSOM SALTS CAN BE APPLIED FOR EXTERNAL USE ONLY.

INACTIVE INGREDIENT

INGREDIENTS: Natural Magnesium Sulfate

STORAGE AND HANDLING

Store in cool, dry place out of direct sunlight. Package sold by weight not volume, some settling may occur during shipment. If caking occurs, tap pouch gently to free granules.